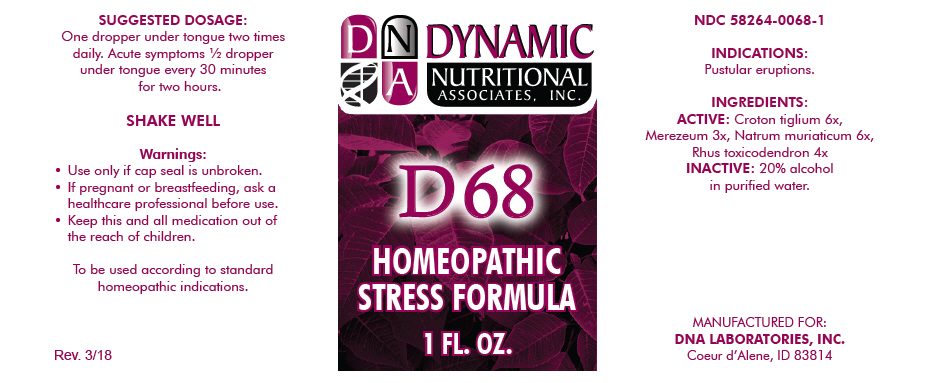 DRUG LABEL: D-68
NDC: 58264-0068 | Form: SOLUTION
Manufacturer: DNA Labs, Inc.
Category: homeopathic | Type: HUMAN OTC DRUG LABEL
Date: 20250113

ACTIVE INGREDIENTS: CROTON OIL 6 [hp_X]/1 mL; DAPHNE MEZEREUM BARK 3 [hp_X]/1 mL; SODIUM CHLORIDE 6 [hp_X]/1 mL; TOXICODENDRON PUBESCENS LEAF 4 [hp_X]/1 mL
INACTIVE INGREDIENTS: ALCOHOL; WATER

D-68

NDC 58264-0068-1

INDICATIONS

PURPOSE

Pustular eruptions.

INGREDIENTS

ACTIVE

Croton tiglium 6x, Merezeum 3x, Natrum muriaticum 6x, Rhus toxicodendron 4x

INACTIVE

20% alcohol in purified water.

SUGGESTED DOSAGE

One dropper under tongue two times daily. Acute symptoms ½ dropper under tongue every 30 minutes for two hours.

STORAGE AND HANDLING

SHAKE WELL

Warnings

- Use only if cap seal is unbroken.

PREGNANCY OR BREAST FEEDING

- If pregnant or breastfeeding, ask a healthcare professional before use.

KEEP OUT OF REACH OF CHILDREN

- Keep this and all medication out of the reach of children.

To be used according to standard homeopathic indications.

PRINCIPAL DISPLAY PANEL - 1 FL. OZ. Bottle Label

DYNAMIC
NUTRITIONAL
ASSOCIATES, INC.

D 68

HOMEOPATHIC
STRESS FORMULA

1 FL. OZ.